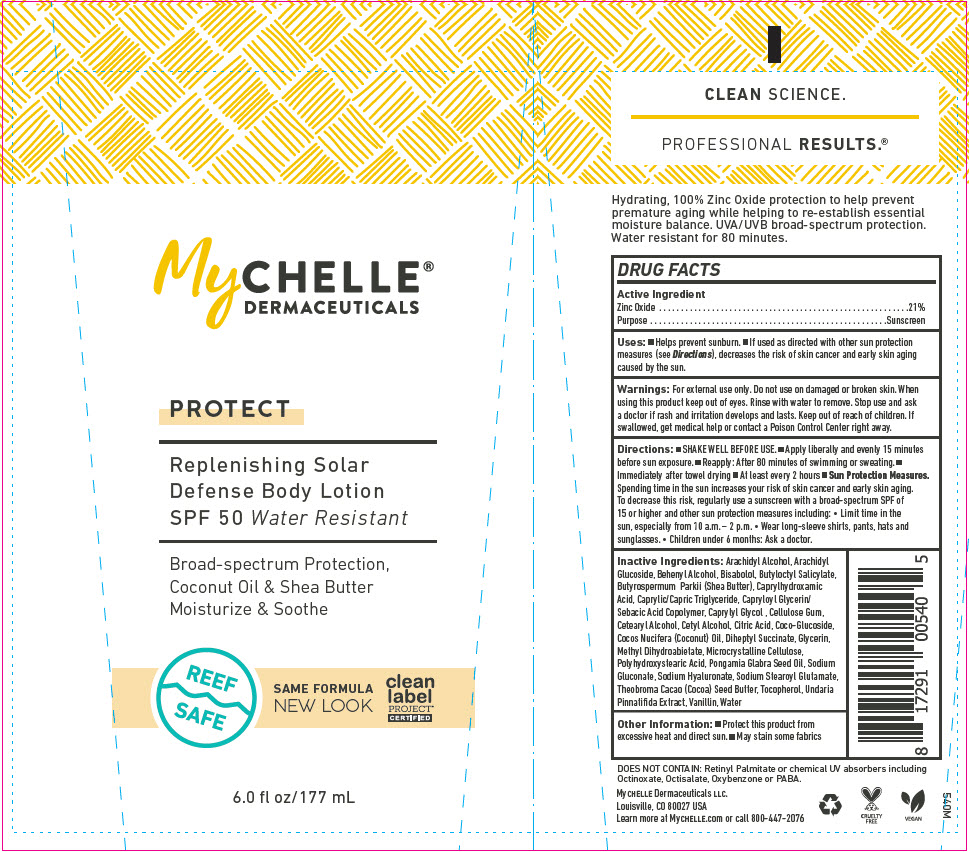 DRUG LABEL: MyChelle Dermaceuticals Replenishing Solar Defense Body SPF 50 
NDC: 72805-021 | Form: LOTION
Manufacturer: French Transit, Ltd.
Category: otc | Type: HUMAN OTC DRUG LABEL
Date: 20220106

ACTIVE INGREDIENTS: Zinc Oxide 21 g/100 mL
INACTIVE INGREDIENTS: WATER; Arachidyl Alcohol; Arachidyl Glucoside; DOCOSANOL; LEVOMENOL; Butyloctyl Salicylate; SHEA BUTTER; Caprylhydroxamic Acid; MEDIUM-CHAIN TRIGLYCERIDES; CAPRYLOYL GLYCERIN/SEBACIC ACID COPOLYMER (2000 MPA.S); Caprylyl Glycol; CARBOXYMETHYLCELLULOSE SODIUM, UNSPECIFIED; CETOSTEARYL ALCOHOL; Cetyl Alcohol; ANHYDROUS CITRIC ACID; Coco Glucoside; COCONUT OIL; Diheptyl Succinate; Glycerin; Methyl Dihydroabietate; Microcrystalline Cellulose; POLYHYDROXYSTEARIC ACID (2300 MW); KARUM SEED OIL; Sodium Gluconate; HYALURONATE SODIUM; Sodium Stearoyl Glutamate; COCOA BUTTER; Tocopherol; UNDARIA PINNATIFIDA; Vanillin

MyChelle® Dermaceuticals Replenishing Solar Defense Body Lotion SPF 50

DRUG FACTS

Active Ingredient

Zinc Oxide 21%

Purpose

Sunscreen

Uses

- Helps prevent sunburn.
- If used as directed with other sun protection measures (see Directions), decreases the risk of skin cancer and early skin aging caused by the sun.

Warnings

For external use only. Do not use on damaged or broken skin. When using this product keep out of eyes. Rinse with water to remove. Stop use and ask a doctor if rash and irritation develops and lasts.

Keep out of reach of children. If swallowed, get medical help or contact a Poison Control Center right away.

Directions

- SHAKE WELL BEFORE USE.
- Apply liberally and evenly 15 minutes before sun exposure.
- Reapply: After 80 minutes of swimming or sweating.
- Immediately after towel drying
- At least every 2 hours
- Sun Protection Measures. Spending time in the sun increases your risk of skin cancer and early skin aging. To decrease this risk, regularly use a sunscreen with a broad-spectrum SPF of 15 or higher and other sun protection measures including:
  - Limit time in the sun, especially from 10 a.m. – 2 p.m.
  - Wear long-sleeve shirts, pants, hats and sunglasses.
  - Children under 6 months: Ask a doctor.

Inactive Ingredients

Arachidyl Alcohol, Arachidyl Glucoside, Behenyl Alcohol, Bisabolol, Butyloctyl Salicylate, Butyrospermum Parkii (Shea Butter), Caprylhydroxamic Acid, Caprylic/Capric Triglyceride, Capryloyl Glycerin/ Sebacic Acid Copolymer, Caprylyl Glycol , Cellulose Gum, Cetearyl Alcohol, Cetyl Alcohol, Citric Acid, Coco-Glucoside, Cocos Nucifera (Coconut) Oil, Diheptyl Succinate, Glycerin, Methyl Dihydroabietate, Microcrystalline Cellulose, Polyhydroxystearic Acid, Pongamia Glabra Seed Oil, Sodium Gluconate, Sodium Hyaluronate, Sodium Stearoyl Glutamate, Theobroma Cacao (Cocoa) Seed Butter, Tocopherol, Undaria Pinnatifida Extract, Vanillin, Water

Other Information

- Protect this product from excessive heat and direct sun.
- May stain some fabrics

PRINCIPAL DISPLAY PANEL - 177 mL Tube Label

MyCHELLE®
DERMACEUTICALS

PROTECT

Replenishing Solar
Defense Body Lotion
SPF 50 Water Resistant

Broad-spectrum Protection,
Coconut Oil & Shea Butter
Moisturize & Soothe

REEF
SAFE

SAME FORMULA
NEW LOOK

clean
label
PROJECT®
CERTIFIED

6.0 fl oz/177 mL